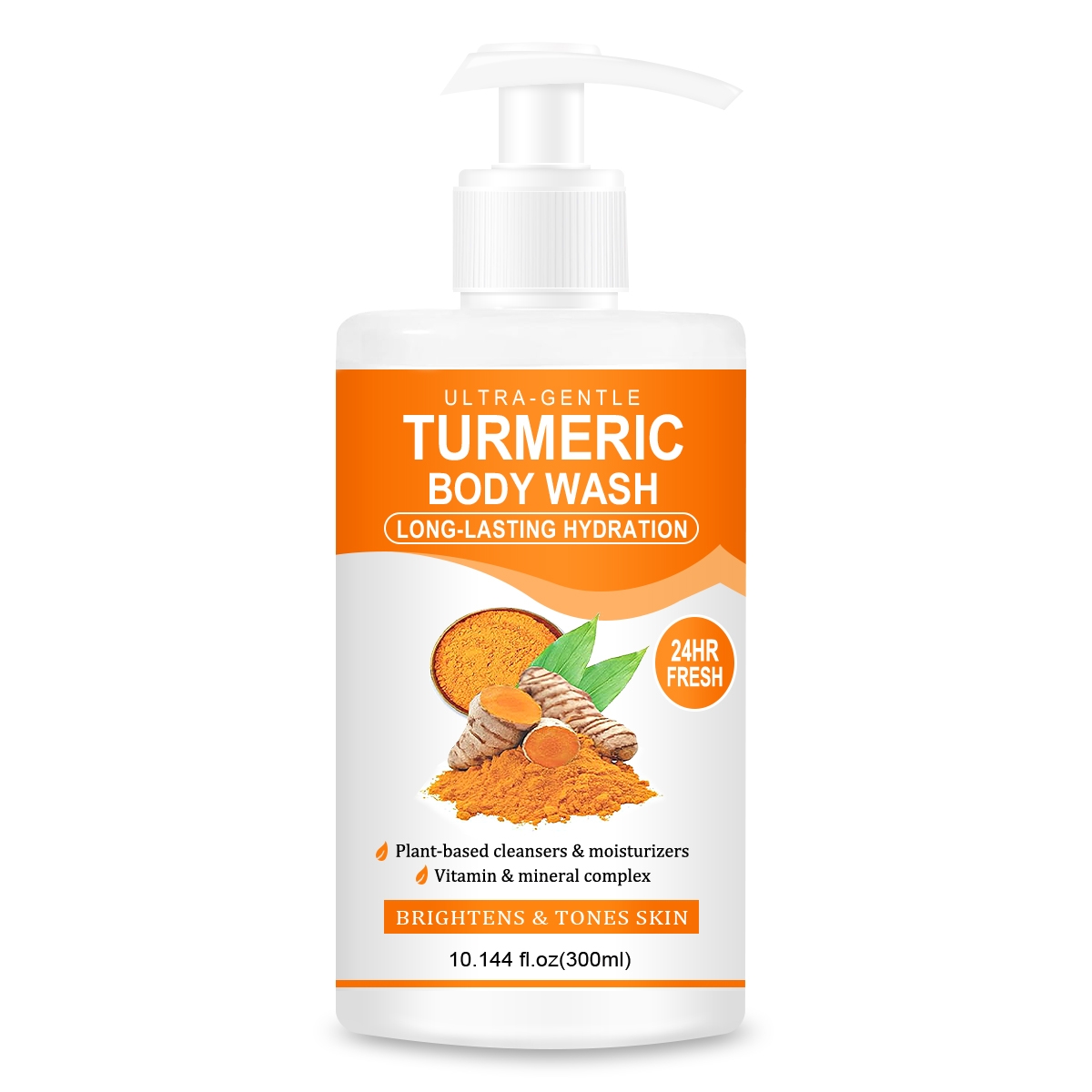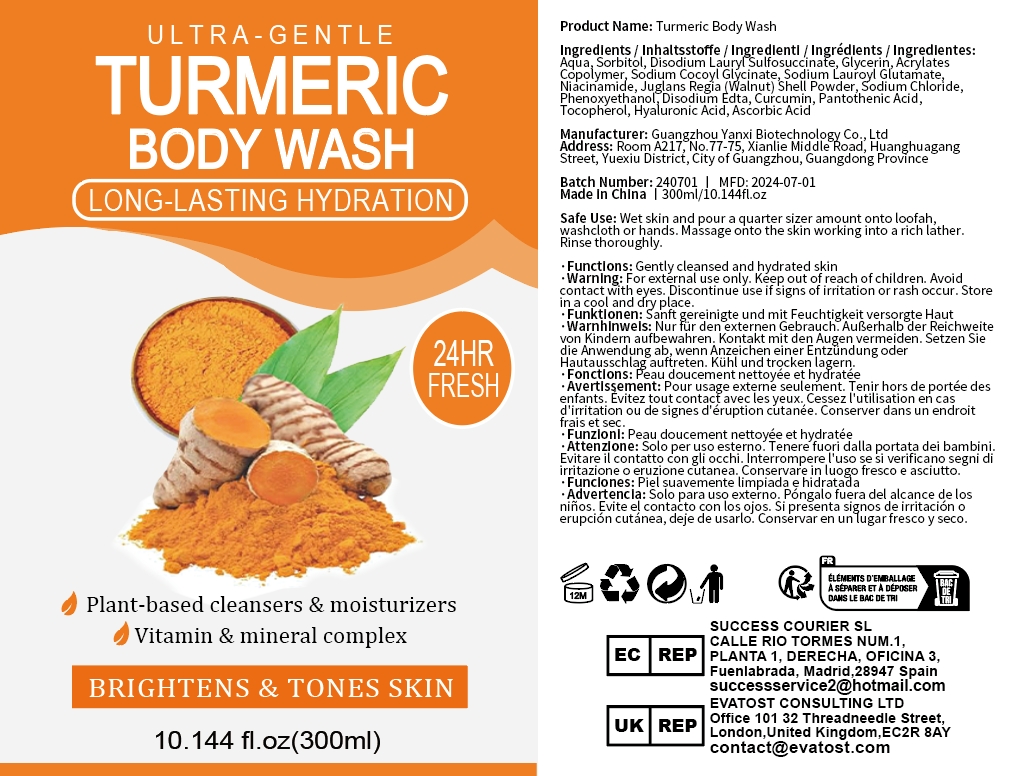 DRUG LABEL: Turmeric Body Wash
NDC: 84025-252 | Form: CREAM
Manufacturer: Guangzhou Yanxi Biotechnology Co., Ltd
Category: otc | Type: HUMAN OTC DRUG LABEL
Date: 20241108

ACTIVE INGREDIENTS: TOCOPHEROL 13 mg/300 mL; SORBITOL 15 mg/300 mL
INACTIVE INGREDIENTS: WATER

DOSAGE AND ADMINISTRATION

Wet skin and pour a quarter sizer amount onto loofah,washcloth or hands. Massage onto the skin working into a rich lather.Rinse thoroughly.

WARNINGS

Keep out of children

INACTIVE INGREDIENT

Aqua

INDICATIONS AND USAGE

For daily skin care

Keep out of children

PURPOSE

Brightens and tones skin